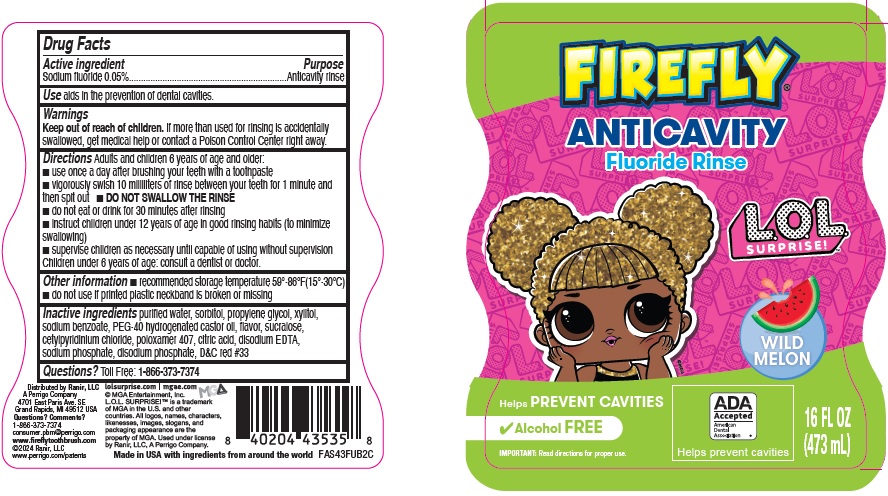 DRUG LABEL: Firefly Anticavity Fluoride
NDC: 66923-007 | Form: RINSE
Manufacturer: Ranir LLC
Category: otc | Type: HUMAN OTC DRUG LABEL
Date: 20241125

ACTIVE INGREDIENTS: SODIUM FLUORIDE .5 mg/1 mL
INACTIVE INGREDIENTS: WATER; SORBITOL; PROPYLENE GLYCOL; XYLITOL; SODIUM BENZOATE; POLYOXYL 40 HYDROGENATED CASTOR OIL; SUCRALOSE; CETYLPYRIDINIUM CHLORIDE; POLOXAMER 407; CITRIC ACID MONOHYDRATE; EDETATE DISODIUM ANHYDROUS; SODIUM PHOSPHATE; SODIUM PHOSPHATE, DIBASIC, ANHYDROUS; D&C RED NO. 33

FIREFLY Anticavity Fluoride Rinse L.O.L. Surprise! Drug Facts

Active ingredient

Sodium Fluoride 0.05%

Purpose

Anticavity rinse

Use

aids in the prevention of dental cavities.

Warnings

Keep out of reach of children.

If more than used for rinsing is accidentally swallowed, get medical help or contact a Poison Control Center right away.

Directions

Adults and children 6 years of age and older:

- use once a day after brushing your teeth with a toothpaste
- vigorously swish 10 milliliters of rinse between your teeth for 1 minute and then spit out
- DO NOT SWALLOW THE RINSE
- do not eat or drink for 30 minutes after rinsing
- instruct children under 12 years of age in good rinsing habits (to minimize swallowing)
- supervise children as necessary until capable of using without supervision
  Children under 6 years of age: consult a dentist or doctor.

Other Information

- recommended storage temperature 59°-86°F(15°-30°C)
- do not use if printed plastic neckband is broken or missing

Inactive Ingredients

purified water, sorbitol, propylene glycol, xylitol, sodium benzoate, PEG-40 hydrogenated castor oil, flavor, sucralose, cetylpyridinium chloride, poloxamer 407, citric acid, disodium EDTA, sodium phosphate, disodium phosphate, D&C red #33

Questions?

Toll Free: 1-866-373-7374

Principal Display Panel

FIREFLY® ANTICAVITY Fluoride Rinse

L.O.L. SURPRISE!™

WILD MELON

Helps PREVENT CAVITIES

ADA Accepted American Dental Association®

Helps prevent cavities

Alcohol FREE

IMPORTANT: Read directions for proper use.

16 FL OZ (473 mL)